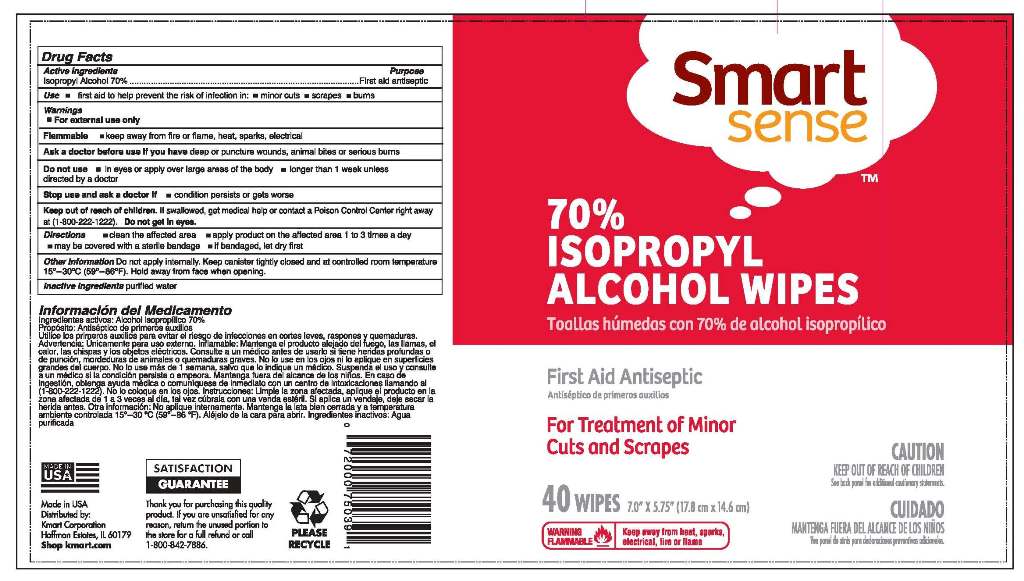 DRUG LABEL: Smart Sense Isopropyl Alcohol Wipes
NDC: 52553-001 | Form: CLOTH
Manufacturer: US Nonwovens
Category: otc | Type: HUMAN OTC DRUG LABEL
Date: 20110829

ACTIVE INGREDIENTS: ISOPROPYL ALCOHOL 0.7 mL/1 mL
INACTIVE INGREDIENTS: WATER

Smart Sense 70% Isopropyl Alcohol Wipes

PRINCIPAL DISPLAY PANEL

Smart Sense

70% Isopropyl Alcohol Wipes

First Aid Antiseptic

For Treatment of Minor Cuts and Scrapes

40 Wipes

CAUTION

KEEP OUT OF REACH OF CHILDREN

DRUG FACTS

Active Ingredients

Isopropyl Alcohol 70%

INDICATIONS AND USAGE

Use - First Aid to help prevent infection in: - minor cuts - scrapes - burns

Purpose

First Aid Antiseptic

Warnings
- For External Use Only
Flammable
- Keep away from fire or flame, heat, sparks, electrical

Ask a doctor before use if you have deep or puncture wounds, animal bites, or serious burns

Do not use - in eyes or over large areas of the body - longer than one week unless directed by a doctor

Keep out of reach of children. If swallowed, get medical help or contact a Poison Control Center right away

at (1-800-222-1222). Do not get in eyes.

INDICATIONS AND USAGE

Directions - clean the affected area - apply product on the affected area 1 to 3 times a day

- may be covered with a sterile bandage - if bandaged, let dry first

Other Information Do not apply internally, Keep canister tightly closed and at a controlled room temperature

15o- 30oC (59o-86oF). Hold away from face when opening.

Inactive Ingredients purified water